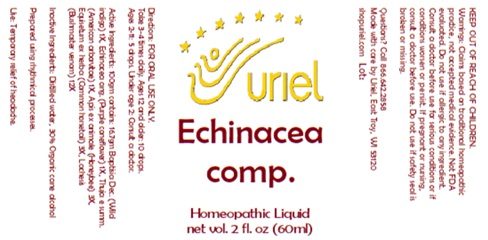 DRUG LABEL: Echinacea comp.
NDC: 48951-4192 | Form: LIQUID
Manufacturer: Uriel Pharmacy, Inc
Category: homeopathic | Type: HUMAN OTC DRUG LABEL
Date: 20241127

ACTIVE INGREDIENTS: THUJA OCCIDENTALIS WHOLE 1 [hp_X]/1 mL; LACHESIS MUTA VENOM 12 [hp_X]/1 mL; ECHINACEA ANGUSTIFOLIA 1 [hp_X]/1 mL; APIS MELLIFERA 3 [hp_X]/1 mL; EQUISETUM ARVENSE TOP 3 [hp_X]/1 mL; BAPTISIA AUSTRALIS ROOT 1 [hp_X]/1 mL
INACTIVE INGREDIENTS: ALCOHOL; WATER

Echinacea comp.

INDICATIONS AND USAGE

Directions: FOR ORAL USE ONLY.

DOSAGE AND ADMINISTRATION

Take 3-4 times daily. Ages 12 and older: 10 drops.
Ages 2-11: 5 drops. Under age 2: Consult a doctor.

ACTIVE INGREDIENT

Active Ingredients: 100gm contains: 16.7gm Baptisia Dec. (Wild indigo) 1X, Echinacea ang. (Purple coneflower) 1X, Thuja e summ. (American arborvitae) 1X, Apis ex animale (Honeybee) 3X, Equisetum ex herba (Common horsetail) 3X, Lachesis (Bushmaster venom) 12X

Inactive Ingredients: Distilled water, 30% Organic cane alcohol

Prepared using rhythmical processes.

PURPOSE

Use: Temporary relief of headache.

KEEP OUT OF REACH OF CHILDREN.

WARNINGS

Warnings: Claims based on traditional homeopathic practice, not accepted medical evidence. Not FDA evaluated. Do not use if allergic to any ingredient. Consult a doctor before use for serious conditions or if conditions worsen or persist. If pregnant or nursing, consult a doctor before use. Do not use if safety seal is broken or missing.

Questions? Call 866.642.2858
Made with care by Uriel, East Troy, WI 53120
shopuriel.com Lot: